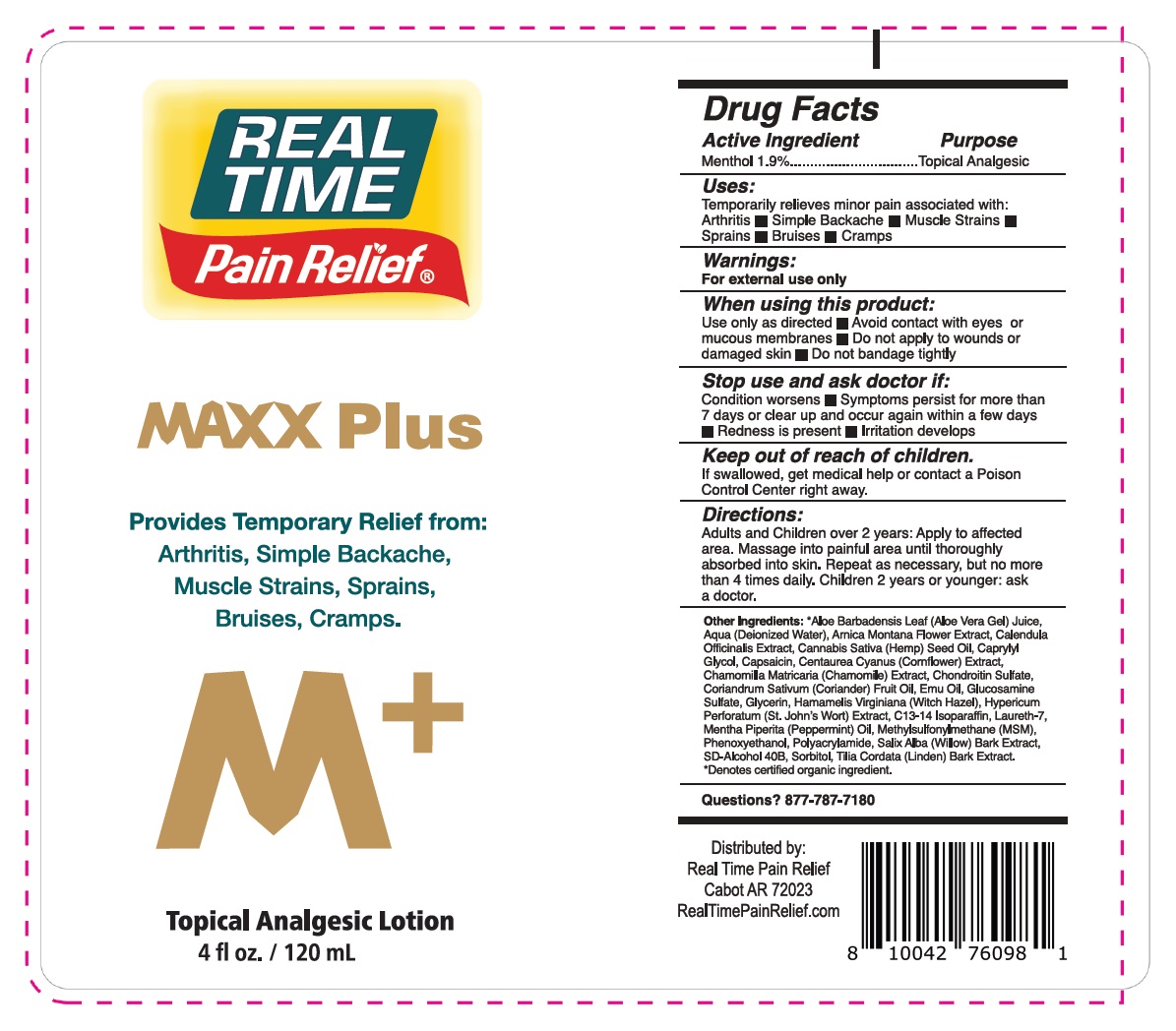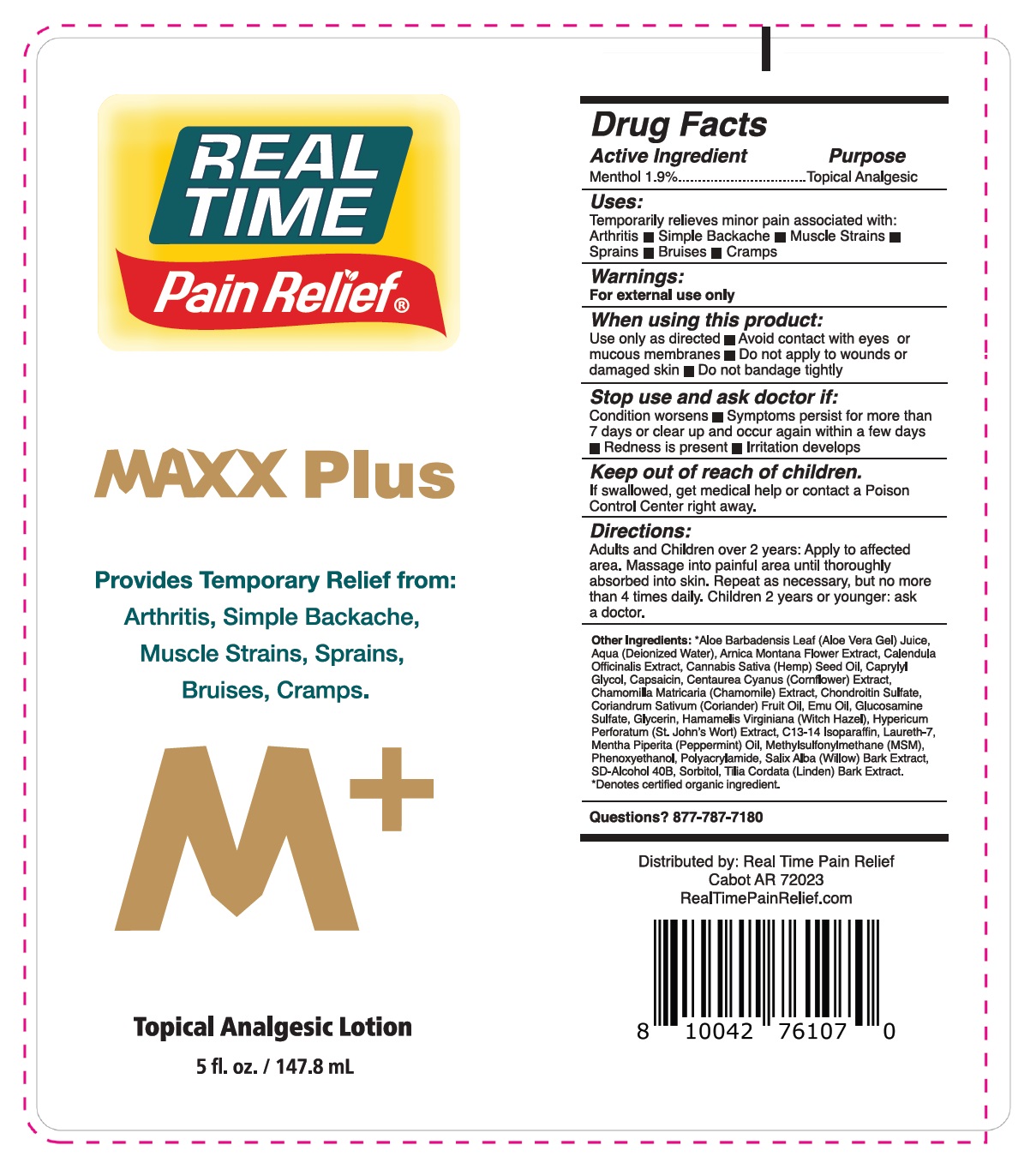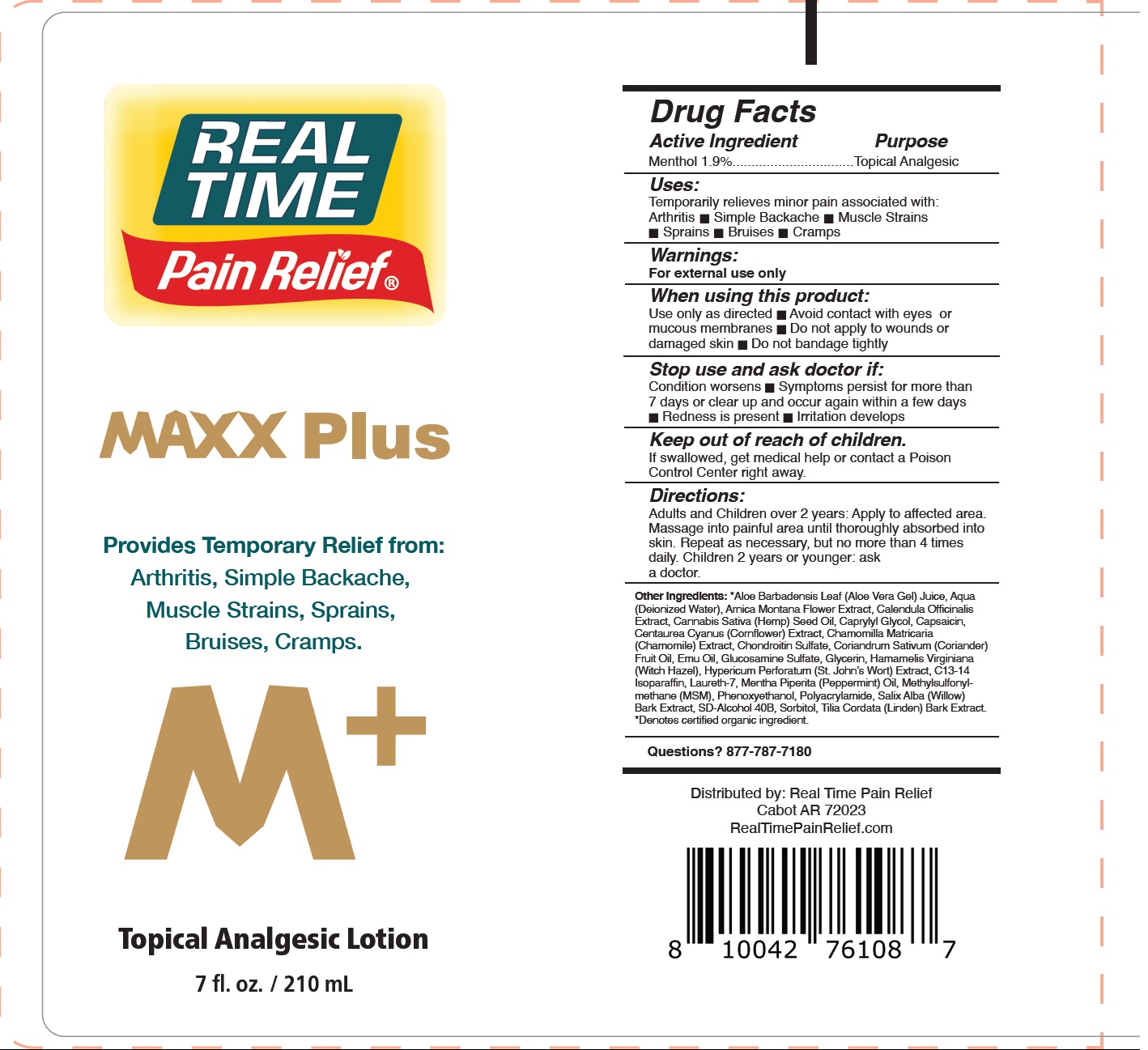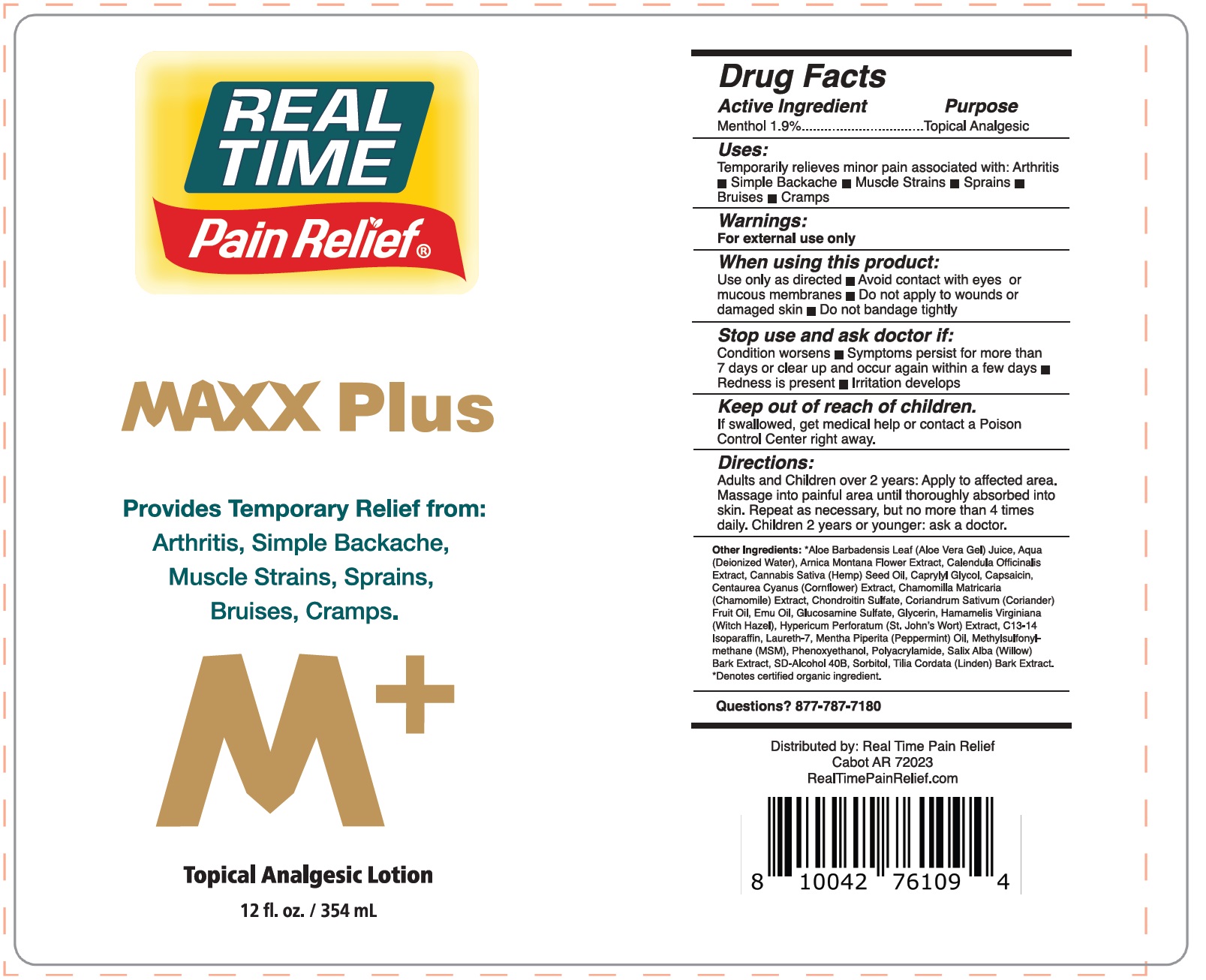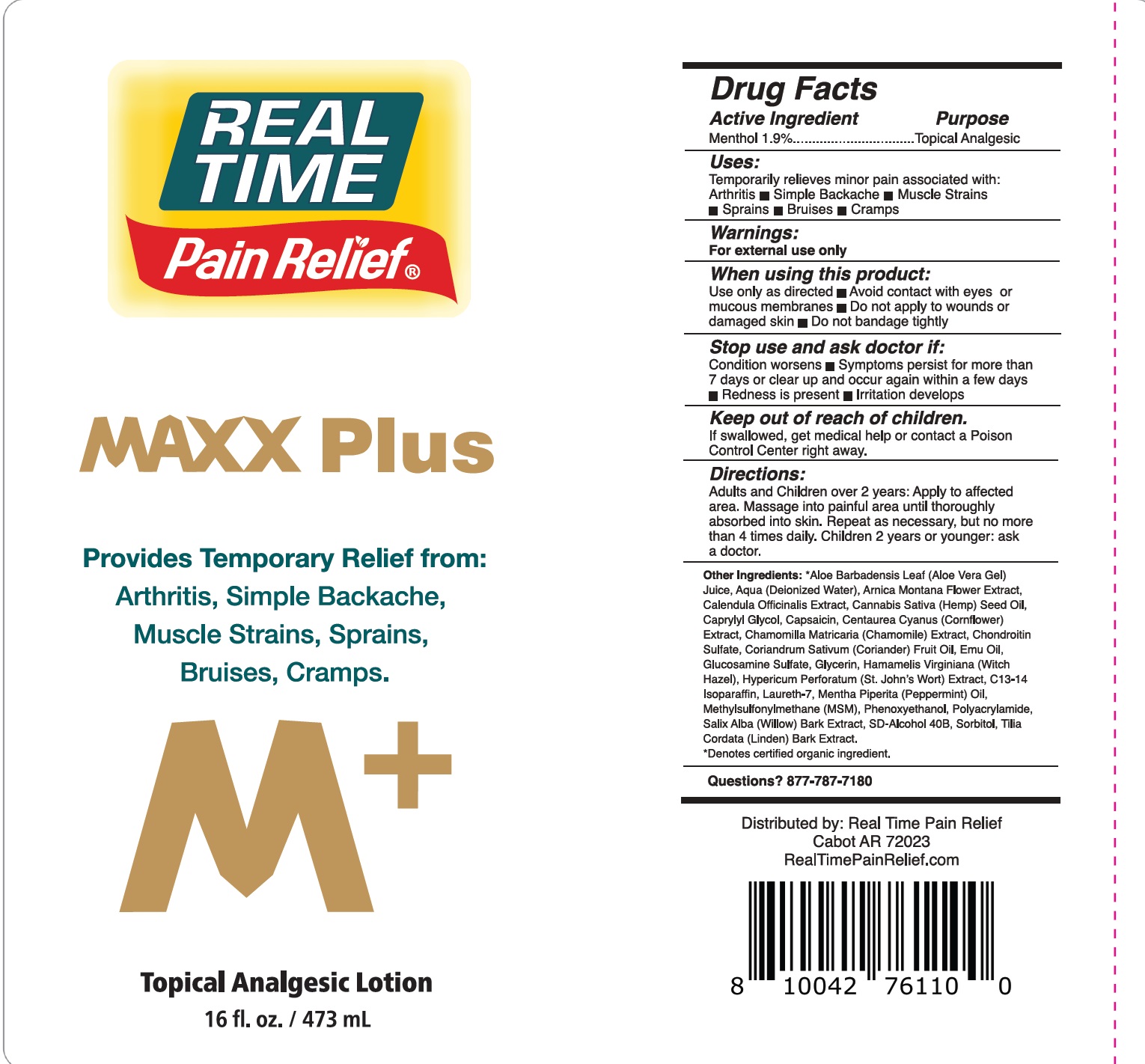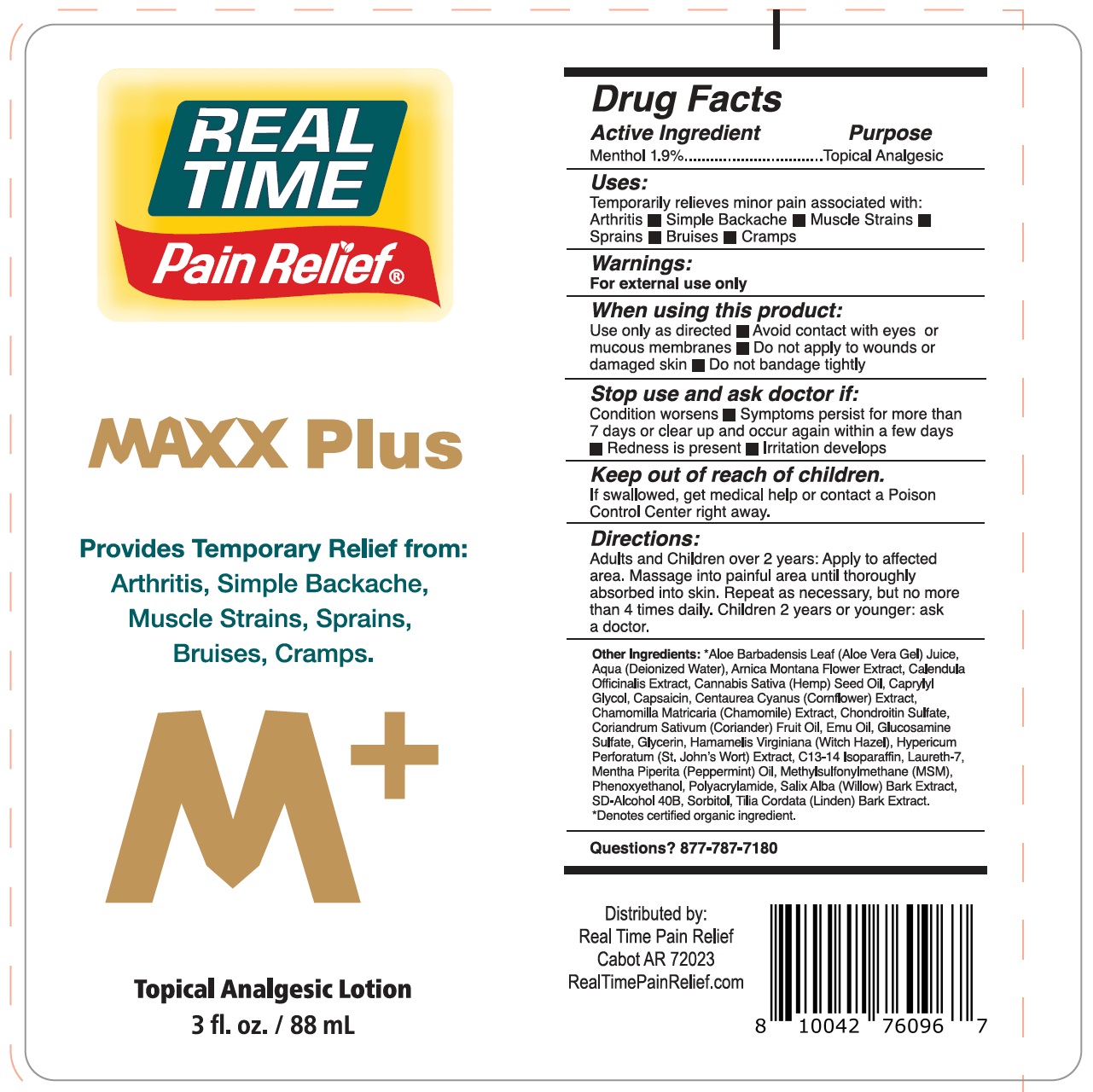 DRUG LABEL: Real Time Pain Relief Maxx Plus Topical Analgesic
NDC: 84573-547 | Form: LOTION
Manufacturer: Real Time Products Inc.
Category: otc | Type: HUMAN OTC DRUG LABEL
Date: 20241112

ACTIVE INGREDIENTS: MENTHOL 19 mg/1 mL
INACTIVE INGREDIENTS: ALOE VERA LEAF; WATER; ARNICA MONTANA FLOWER; CALENDULA OFFICINALIS FLOWER; HEMP; CAPRYLYL GLYCOL; CAPSAICIN; CHAMOMILE; CORIANDER OIL; EMU OIL; GLUCOSAMINE SULFATE; GLYCERIN; WITCH HAZEL; ST. JOHN'S WORT; C13-14 ISOPARAFFIN; LAURETH-7; PEPPERMINT OIL; DIMETHYL SULFONE; PHENOXYETHANOL; SALIX ALBA (WILLOW) BARK EXTRACT; SORBITOL

Real Time Pain Relief Maxx Plus Topical Analgesic Lotion

Active Ingredient

Menthol 1.9%

Purpose

Topical Analgesic

Uses:

Temporarily relieves minor pain associated with: Arthritis

- Simple Backache
- Muscle Strains
- Sprains
- Bruises
- Cramps

Warnings:

For external use only

When using this product:

Use only as directed

- Avoid contact with eyes or mucous membranes
- Do not apply to wounds or damaged skin
- Do not bandage tightly

Stop use and ask a doctor if:

Condition worsens

- Symptoms persist for more than 7 days or clear up and occur again within a few days
- Redness is present
- Irritation develops

Keep out of reach of children.

If swallowed, get medical help or contact a Poison Control Center right away.

Directions:

Adults and Children over 2 years: Apply to affected area. Massage into painful area until thoroughly absorbed into skin. Repeat as necessary, but no more than 4 times daily. Children 2 years or younger: ask a doctor.

Other Ingredients:

*Aloe Barbadensis Leaf (Aloe Vera Gel) Juice, Aqua (Deionized Water), Arnica Montana Flower Extract, Calendula Officinalis Extract, Cannabis Sativa (Hemp)Seed Oil, Caprylyl Glycol, Capsaicin, Centaurea Cyanus (Cornflower) Extract, Chamomilla Matricaria (Chamomile) Extract, Chondroitin Sulfate, Coriandrum Sativum (Coriander) Fruit Oil, Emu Oil, Glucosamine Sulfate, Glycerin, Hamamelis Virginiana (Witch Hazel), Hypericum Perforatum (St. John's Wort) Extract, C13-14 Isoparaffin, Laureth-7, Mentha Piperita (Peppermint) Oil, Methylsulfonylmethane (MSM), Phenoxyethanol, Polyacrylamide, Salix Alba (Willow) Bark Extract, SD-Alcohol 40B, Sorbitol, Tilia Cordata (Linden) Bark Extract. *Denotes certified organic ingredient.

Questions?

877-787-7180